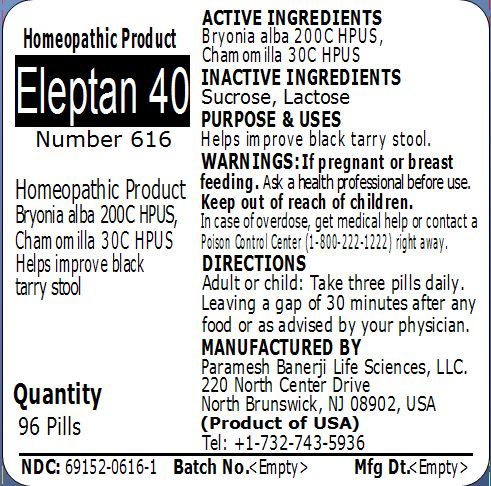 DRUG LABEL: Eleptan 40 Number 616
NDC: 69152-0616 | Form: PELLET
Manufacturer: Paramesh Banerji Life Sciences LLC
Category: homeopathic | Type: HUMAN OTC DRUG LABEL
Date: 20150302

ACTIVE INGREDIENTS: BRYONIA ALBA ROOT 200 [hp_C]/1 1; MATRICARIA RECUTITA 30 [hp_C]/1 1
INACTIVE INGREDIENTS: SUCROSE; LACTOSE

Active Ingredients

Bryonia alba 200C HPUS, Chamomilla 30C HPUS

Inactive Ingredients

Sucrose, Lactose

Purpose

Helps improve black tarry stool

Uses

Helps improve black tarry stool

Warnings

If pregnant or breast feeding ask a health professional before use.

Keep out of reach of children. In case of overdose, get medical help or contact a Poison Control Center (1-800-222-1222) right away.

Direction

Adult or child: Take three pills daily. Leaving a gap of 30 minutes after any food or as advised by your physician.

Manufactured by

Paramesh Banerji Life Sciences, LLC

220 North Center Drive

North Brunswick, NJ 08902, USA

Product of USA

Tel: +1-732-743-5936

Principal Display Panel

Homeopathic Product

Eleptan 40

Number 616

Homeopathic Product

Bryonia alba 200C HPUS, Chamomilla 30C HPUS

Helps improve black tarry stool

Quantity

96 Pills